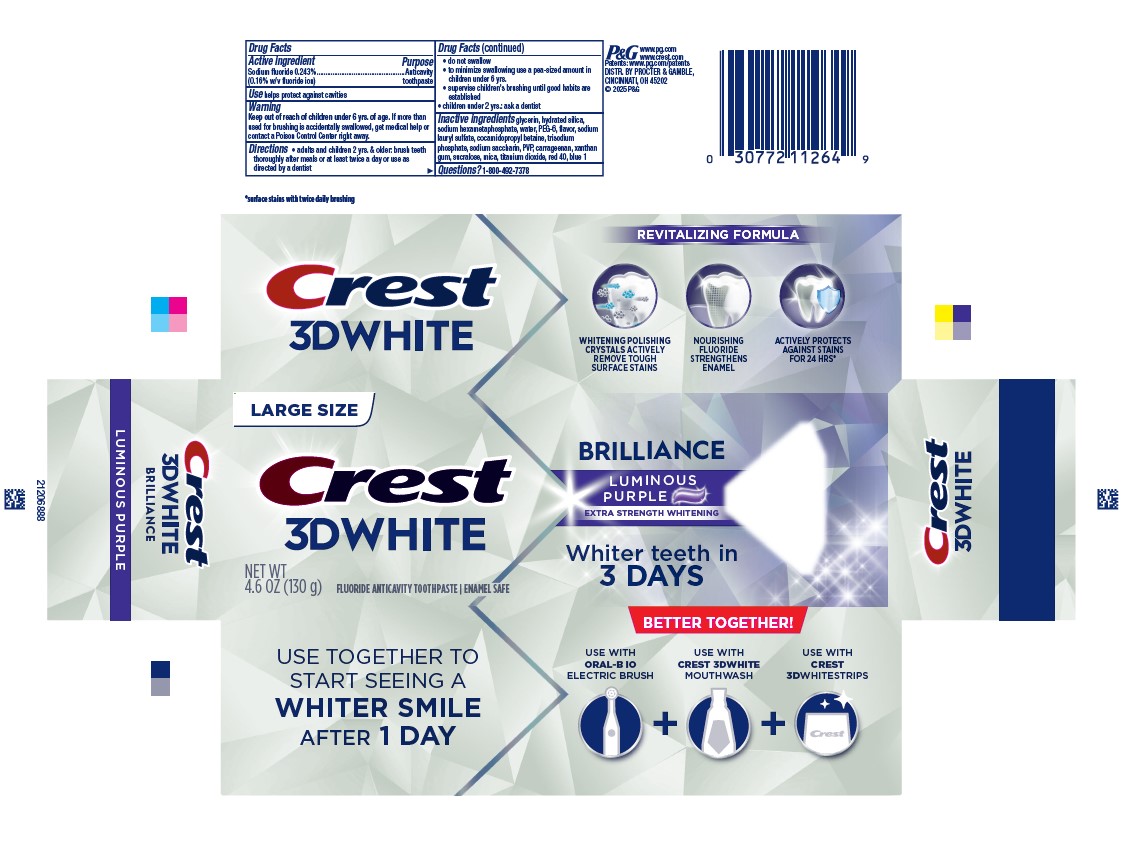 DRUG LABEL: Crest
NDC: 69423-787 | Form: PASTE, DENTIFRICE
Manufacturer: The Procter & Gamble Manufacturing Company
Category: otc | Type: HUMAN OTC DRUG LABEL
Date: 20250930

ACTIVE INGREDIENTS: SODIUM FLUORIDE 1.6 mg/1 g
INACTIVE INGREDIENTS: FD&C RED NO. 40; SODIUM POLYMETAPHOSPHATE; POLYETHYLENE GLYCOL 300; COCAMIDOPROPYL BETAINE; CARRAGEENAN; SUCRALOSE; HYDRATED SILICA; POVIDONE, UNSPECIFIED; XANTHAN GUM; GLYCERIN; FD&C BLUE NO. 1; WATER; SACCHARIN SODIUM; MICA; TITANIUM DIOXIDE; SODIUM LAURYL SULFATE; SODIUM PHOSPHATE, TRIBASIC, ANHYDROUS

Crest 3D White Brilliance Luminous Purple

Drug Facts

Active ingredient

Sodium fluoride 0.243% (0.15% w/v fluoride ion)

Purpose

Anticavity toothpaste

Use

helps protect against cavities

Warning

Keep out of reach of children under 6 yrs. of age. If more than used for brushing is accidentally swallowed, get medical help or contact a Poison Control Center right away.

Directions

- adults and children 2 yrs. & older: brush teeth thoroughly after meals or at least twice a day or use as directed by a dentist
- do not swallow
- to minimize swallowing use a pea-sized amount in children under 6
- supervise children's brushing until good habits are established
- children under 2 yrs.: ask a dentist

Inactive ingredients

glycerin, hydrated silica, sodium hexametaphosphate, water, PEG-6, flavor, sodium
lauryl sulfate, cocamidopropyl betaine, trisodium phosphate, sodium saccharin, PVP, carrageenan, xanthan gum, sucralose, mica, titanium dioxide, red 40, blue 1

Questions?

1-800-492-7378

DISTR. BY PROCTER & GAMBLE, CINCINNATI, OH 45202

PRINCIPAL DISPLAY PANEL - 130 g Tube Carton

LARGE SIZE

CREST

3D WHITE

BRILLIANCE

LUMINOUS PURPLE

EXTRA STRENGTH WHITENING

net wt 4.6 oz (130 g)

FLUORIDE ANTICAVITY TOOTHPASTE

ENAMEL SAFE

WHITER TEETH IN 3 DAYS